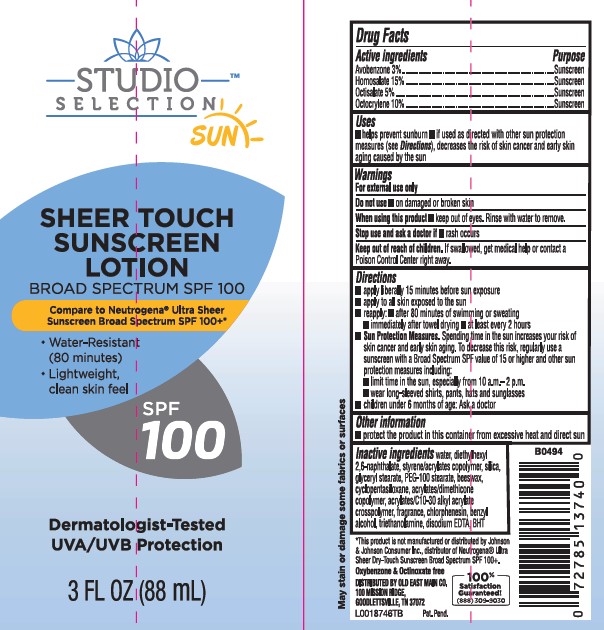 DRUG LABEL: SUNSCREEN
NDC: 55910-877 | Form: LOTION
Manufacturer: Old East Main Co.
Category: otc | Type: HUMAN OTC DRUG LABEL
Date: 20260302

ACTIVE INGREDIENTS: AVOBENZONE 30 mg/1 mL; HOMOSALATE 150 mg/1 mL; OCTISALATE 50 mg/1 mL; OCTOCRYLENE 100 mg/1 mL
INACTIVE INGREDIENTS: WATER; DIETHYLHEXYL 2,6-NAPHTHALATE; STYRENE/ACRYLAMIDE COPOLYMER (500000 MW); SILICON DIOXIDE; GLYCERYL MONOSTEARATE; PEG-100 STEARATE; YELLOW WAX; CYCLOMETHICONE 5; CARBOMER INTERPOLYMER TYPE A (ALLYL SUCROSE CROSSLINKED); CHLORPHENESIN; BENZYL ALCOHOL; TROLAMINE; EDETATE DISODIUM ANHYDROUS; BUTYLATED HYDROXYTOLUENE

Studio Selection 922.000/922AA
Sheer Touch Sunscreen SPF 100

Active ingredients

Avobenzone 3%
Homosalate 15%
Octisalate 5%
Octocrylene 10%

Purpose

sunscreen

Uses

- helps prevent sunburn
- if used as directed with other sun protection measures (see Directions), decreases the risk of skin cancer and early skin aging caused by the sun

Warnings

For external use only

Do not use

on damaged or broken skin

When using this product

- keep out of eyes. Rinse with water to remove.

Stop use and ask a doctor if

- rash occurs

Keep out of reach of children.

If swallowed, get medical help or contact a Poison Control Center right away.

Directions

- apply liberally 15 minutes before sun exposure
- apply to all skin exposed to the sun
- reapply:
- after 80 minutes of swimming or sweating
- immediately after towel drying
- at least every 2 hours
- Sun Protection Measures.Spending time in the sun increases your risk of skin cancer and early skin aging. To decrease this risk, regularly use a sunscreen with a Broad Spectrum SPF value of 15 or higher and other sun protection measures including:
- limit time in the sun, especially from 10 a.m.–2 p.m.
- wear long-sleeved shirts, pants, hats and sunglasses
- children under 6 months of age: Ask a doctor

Other information

- protect the product in this container from excessive heat and direct sun

Inactive ingredients

water, diethylhexyl 2,6-naphthalate, styrene/acrylates copolymer, silica, glyceryl stearate, PEG-100 stearate, beeswax, cyclopentasiloxane, acrylates/dimethicone copolymer, acrylates/C10-30 alkyl acrylate crosspolymer, fragrance, chlorphenesin, benzyl alcohol, triethanolamine, disodium EDTA, BHT

Disclaimers

May stain or damage some fabrics or surfaces

*This product is not manufactured or distributed by Johnson & Johnson Consumer Inc., distributor of Neutrogena®Ultra Sheer Dry-Touch Sunscreen Broad Spectrum SPF 100+.

Oxybenzone & Octinoxate free

ADVERSE REACTION

DISTRIBUTED BY OLD EAST MAIN CO.

100 MISSION RIDGE

GOODLETTSVILLE, TN 37072

100% Satisfaction Guaranteed!

(888) 309-9030

principal display panel

STUDIO SELECTION™

SUN

SHEER TOUCH

SUNSCREEN LOTION

BROAD SPECTRUM SPF 100

Compare to Neutrogena®Ultra Sheer Sunscreen Broad Spectrum SPF 100+*

- Water-Resistant (80 minutes)
- Lightweight, Clean skin feel

SPF 100

Dermatologist-Tested

UVA/UVB Protection

3 FL OZ (88 mL)